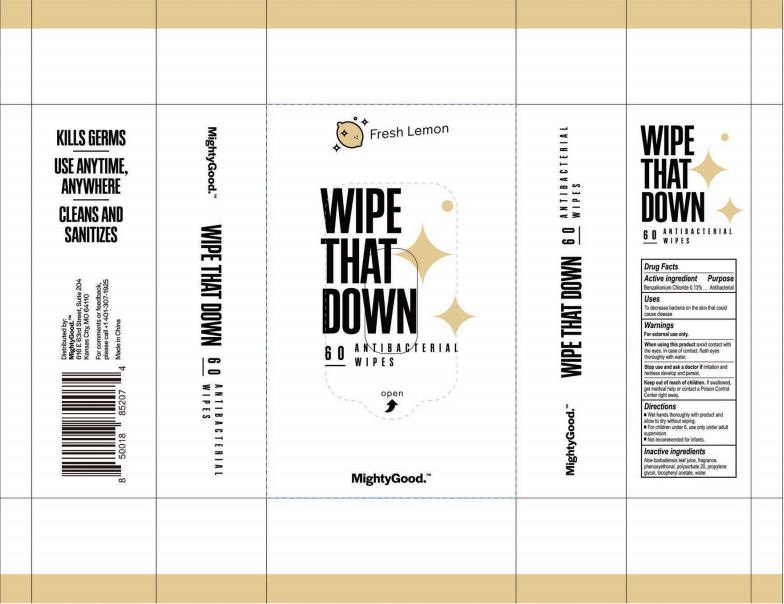 DRUG LABEL: WIPE THAT DOWN 60PCS ANTIBACTERIAL WIPES
NDC: 79650-016 | Form: LIQUID
Manufacturer: Zhangzhou Zhongnan Nursing Products Co., Ltd.
Category: otc | Type: HUMAN OTC DRUG LABEL
Date: 20200928

ACTIVE INGREDIENTS: BENZALKONIUM CHLORIDE 0.13 mg/100 mL
INACTIVE INGREDIENTS: POLYSORBATE 20; FRAGRANCE LEMON ORC2001060; PROPYLENE GLYCOL; ALOE VERA LEAF; WATER; PHENOXYETHANOL; ALPHA-TOCOPHEROL ACETATE

Active Ingredient

Benzalkonium Chloride 0.13%

Purpose

Antibacterial

Uses

To decrease bacteria on the skin that could cause disease

Warnings

For external use only.

When using this product avoid contact with the eyes. In case of contact, flush eyes thoroughly with water.

Stop use and ask a doctor if irritation and redness develop and persist.

Keep out of reach of children. If swallowed, get medical help or contact a Poison Control Center right away.

Directions

- Wet hands thoroughly with product and allow to dry without wiping
- For children under 6, use only under adult supervision
- Not recommended for infants

Other Information

- Keep containers tightly closed in a dry, cool and well-ventilated place.

Inactive Ingredients

Aloe barbadensis leaf juice, fragrance, phenoxyethanol, polysorbate 20, propylene glycol, tocopheryl acetate, water

Package Label/Principal Display Panel

NDC 79650-016-60; 255 mL